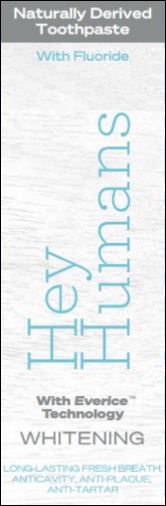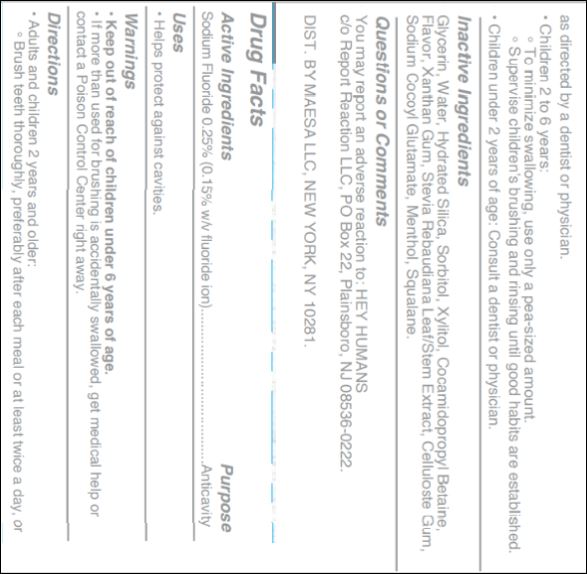 DRUG LABEL: Maesa - Hey Humans
NDC: 73333-199 | Form: PASTE, DENTIFRICE
Manufacturer: Nutrix International, LLC.
Category: otc | Type: HUMAN OTC DRUG LABEL
Date: 20210419

ACTIVE INGREDIENTS: SODIUM FLUORIDE 0.25 g/96 g
INACTIVE INGREDIENTS: MINT 0.008 g/96 g; XANTHAN GUM 0.004 g/96 g; CARBOXYMETHYLCELLULOSE 0.0016 g/96 g; MENTHOL 0.0011 g/96 g; COCAMIDOPROPYL BETAINE 0.01678 g/96 g; GLYCERIN 0.2801 g/96 g; WATER 0.1474 g/96 g; XYLITOL 0.1 g/96 g; STEVIA REBAUDIUNA LEAF 0.0035 g/96 g; SQUALANE 0.00002 g/96 g; SORBITOL 0.25 g/96 g; SILICON DIOXIDE 0.18 g/96 g; SODIUM COCOYL GLUTAMATE 0.005 g/96 g

Active Ingredient

Sodium fluoride 0.25%
(0.15%w/v fluoride ion)

Purpose

Anticavity

Use

Helps protect against cavities.

Warnings

Keep out of reach of children under 6 years of age.

If more than use for brushing is accidentally swallowed, get medical help or contact a Poison Control Center right away

Directions

Adults and children 2 years and older:
Brush teeth thoroughly, preferably after each meal or at least twice a day, or as directed by a dentist or doctor.
Children 2 to 6 years:
To minimize swallowing, use only a pea-size amount.
Supervise Children's brushing and rinsing until good habits are stablished.
Children under 2 years of age:
Consult a dentist or physician.

Inactive Ingredients

Glycerin, water, Hydrate Silica, Sorbitol, Xylitol, Cocomidopropyl Betaine, Flavor, Xanthan Gum, Stevia Rebaudiana leaf/steam extract, Cellulose gum, Sodium cocoyl Glutamate, Menthol and Squalane.

Questions or Comments

You may report an adverse reaction to : Hey Humans c/o Report Reaction LLC, PO Box 22, Plainsboro, NJ 08536-0222
For more Information, please visit www.heyhumans.com

Package, Label

Display Panel